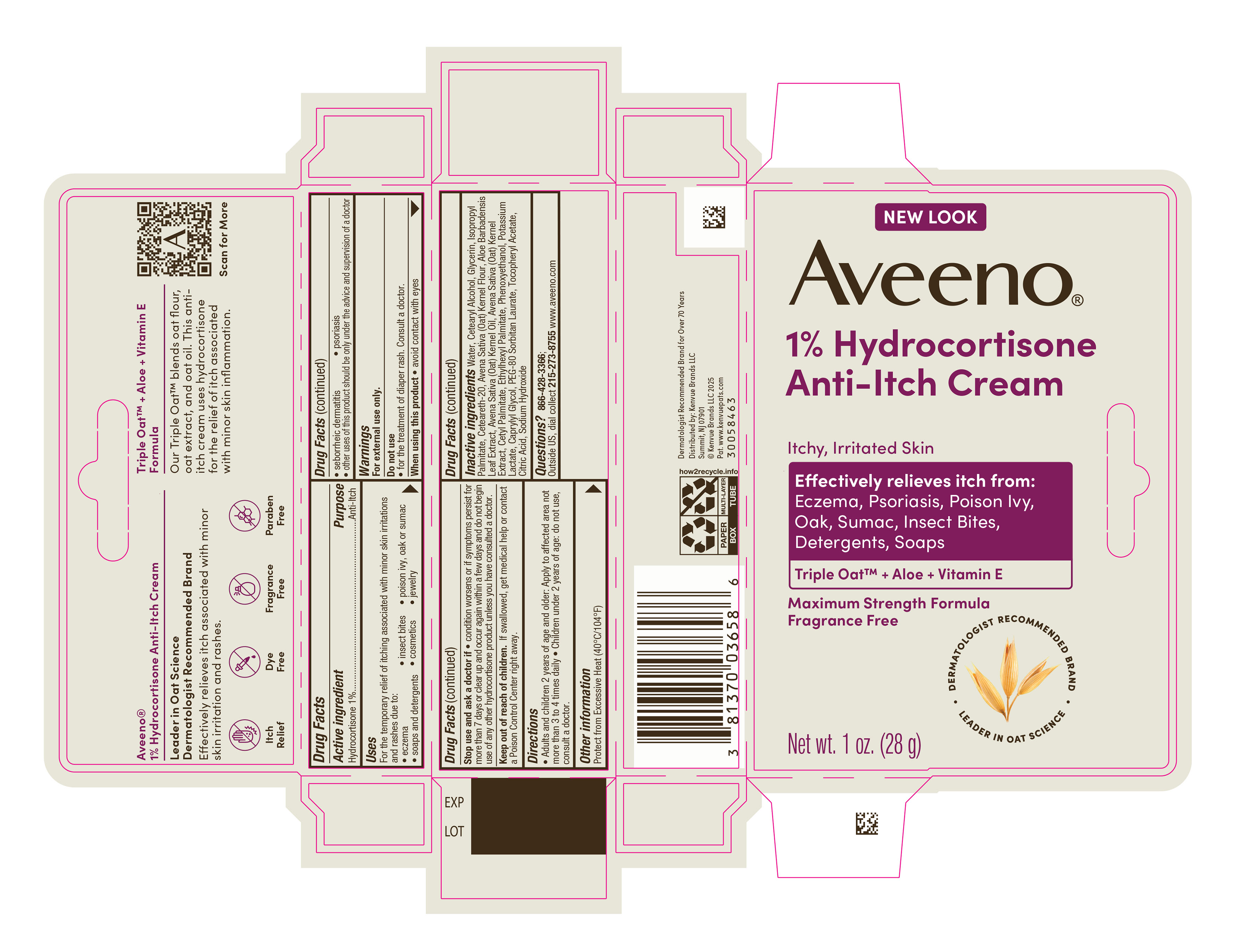 DRUG LABEL: Aveeno 1% Hydrocortisone Anti-Itch Cream
NDC: 69968-0888 | Form: CREAM
Manufacturer: Kenvue Brands LLC
Category: otc | Type: HUMAN OTC DRUG LABEL
Date: 20260122

ACTIVE INGREDIENTS: HYDROCORTISONE 10 mg/1 g
INACTIVE INGREDIENTS: WATER; GLYCERIN; ISOPROPYL PALMITATE; POLYOXYL 20 CETOSTEARYL ETHER; OATMEAL; POTASSIUM LACTATE; ETHYLHEXYL PALMITATE; CETYL PALMITATE; PHENOXYETHANOL; CAPRYLYL GLYCOL; PEG-80 SORBITAN LAURATE; CITRIC ACID MONOHYDRATE; .ALPHA.-TOCOPHEROL ACETATE; ALOE VERA LEAF; OAT; OAT KERNEL OIL; SODIUM HYDROXIDE; CETOSTEARYL ALCOHOL

Aveeno 1% Hydrocortisone Anti-Itch Cream

Drug Facts

Active ingredient

Hydrocortisone 1%

Purpose

Anti-Itch

Uses

For the temporary relief of itching associated with minor skin irritations and rashes due to:

- eczema
- insect bites
- poison ivy, oak or sumac
- soaps and detergents
- cosmetics
- jewelry
- seborrheic dermatitis
- psoriasis
- other uses of this product should be only under the advice and supervision of a doctor

Warnings

For external use only.

Do not use

• for the treatment of diaper rash. Consult a doctor.

When using this product • avoid contact with eyes

Stop use and ask a doctor if • condition worsens or if symptoms persist for more than 7 days or clear up and occur again within a few days and do not begin use of any other hydrocortisone product unless you have consulted a doctor.

Keep out of reach of children. If swallowed, get medical help or contact a Poison Control Center right away.

Directions

- adults and children 2 years of age and older: Apply to affected area not more than 3 to 4 times daily
- children under 2 years of age; do not use, consult a doctor.

Other information

Protect from Excessive Heat (40°C/104°F)

Inactive ingredients

Water, Cetearyl Alcohol, Glycerin, Isopropyl Palmitate, Ceteareth-20, Avena Sativa (Oat) Kernel Flour, Aloe Barbadensis Leaf Extract, Avena Sativa (Oat) Kernel Oil, Avena Sativa (Oat) Kernel Extract, Cetyl Palmitate, Ethylhexyl Palmitate, Phenoxyethanol, Potassium Lactate, Caprylyl Glycol, PEG-80 Sorbitan Laurate, Tocopheryl Acetate, Citric Acid, Sodium Hydroxide

Questions?

866-428-3366;

Outside US, dial collect 215-273-8755 www.aveeno.com

Distributed by:
Kenvue Brands LLC
Summit, NJ 07901

PRINCIPAL DISPLAY PANEL - 28 g Tube Carton Label

NEW LOOK

Aveeno®

1% Hydrocortisone

Anti-Itch Cream

Itchy, Irritated Skin

Effectively relieves itch from:

Eczema, Psoriasis, Poison Ivy,

Oak, Sumac, Insect Bites,

Detergents, Soaps

Triple OatTM + Aloe + Vitamin E

Maximum Strength Formula

Fragrance Free

DERMATOLOGIST RECOMMENDED BRAND

LEADER IN OAT SCIENCE

Net wt. 1 oz. (28 g)